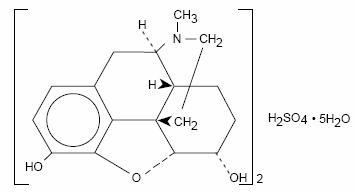 DRUG LABEL: Unknown
Manufacturer: Watson Laboratories, Inc.
Category: prescription | Type: HUMAN PRESCRIPTION DRUG LABELING
Date: 20060412
DEA Schedule: CII

Morphine Sulfate
Extended-Release
Tablets C-II
Rx only
30340-2

DESCRIPTION

Chemically, morphine sulfate is 7,8-didehydro-4,5α-epoxy-17-methylmorphinan-3,6α-diol sulfate (2:1) (salt) pentahydrate and has the following structural formula:

(C17H19NO3)2•H2SO4 Molecular Weight: 668.77

The molecular formula and molecular weight are based on the “anhydrous” form of the drug product

Each extended-release tablet, for oral administration contains 100 mg of morphine sulfate USP. In addition, each tablet contains the following inactive ingredients: cetostearyl alcohol, hydroxyethyl cellulose, hydroxypropyl cellulose, hypromellose, magnesium stearate, polyethylene glycol, polysorbate 80, synthetic black iron oxide, talc and titanium dioxide.

CLINICAL PHARMACOLOGY

Metabolism and Pharmacokinetics

Morphine sulfate extended-release tablets are controlled-release tablets containing morphine sulfate. Following oral administration of a given dose of morphine, the amount ultimately absorbed is essentially the same whether the source is an extended-release or a conventional formulation. Morphine is released from morphine sulfate extended-release tablets somewhat more slowly than from conventional oral preparations. Because of pre-systemic elimination (i.e., metabolism in the gut wall and liver) only about 40% of the administered dose reaches the central compartment.

Once absorbed, morphine is distributed to skeletal muscle, kidneys, liver, intestinal tract, lungs, spleen and brain. Morphine also crosses the placental membranes and has been found in breast milk.

Although a small fraction (less that 5%) of morphine is demethylated, for all practical purposes, virtually all morphine is converted to glucuronide metabolites; among these, morphine-3-glucuronide is present in the highest plasma concentration following oral administration.

The glucuronide system has a very high capacity and is not easily saturated even in disease. Therefore, rate of delivery of morphine to the gut and liver should not influence the total and, probably, the relative quantities of the various metabolites formed. Moreover, even if rate affected the relative amounts of each metabolite formed, it should be unimportant clinically because morphine’s metabolites are ordinarily inactive.

The following pharmacokinetic parameters show considerable inter-subject variation but are representative of average values reported in the literature. The volume of distribution (Vd) for morphine is 4 liters per kilogram, and its terminal elimination half-life is normally 2 to 4 hours.

Following the administration of conventional oral morphine products, approximately fifty percent of the morphine that will reach the central compartment intact reaches it within 30 minutes. Following the administration of an equal amount of morphine sulfate extended-release tablets to normal volunteers, however, this extent of absorption occurs, on average, after 1.5 hours.

The possible effect of food upon the systemic bioavailability of morphine sulfate extended-release tablets has not been systematically evaluated for all strengths. Data from at least one study suggests that concurrent administration of morphine sulfate extended-release tablets with a fatty meal may cause a slight decrease in peak plasma concentration.

Variation in the physical/mechanical properties of a formulation of an oral morphine drug product can affect both its absolute bioavailability and its absorption rate constant (ka). The formulation employed in morphine sulfate extended-release tablets have not been shown to affect morphine’s oral bioavailability, but does decrease its apparent Ka. Other basic pharmacokinetic parameters (e.g., volume of distribution [Vd], elimination rate constant [Ke], clearance [CI]), are unchanged as they are fundamental properties of morphine in the organism. However, in chronic use, the possibility that shifts in metabolite to parent drug ratios may occur cannot be excluded.

When immediate-release oral morphine or morphine sulfate extended-release tablets are given on a fixed dosing regimen, steady state is achieved in about a day.

For a given dose and dosing interval, the AUC and average blood concentration of morphine at steady state (Css) will be independent of the specific type of oral formulation administered so long as the formulations have the same absolute bioavailability. The absorption rate of a formulation will, however, affect the maximum (Cmax) and minimum (Cmin) blood levels and the times of their occurrence.

Pharmacodynamics

The effects described below are common to all morphine-containing products.

Central Nervous System

The principal actions of therapeutic value of morphine are analgesia and sedation (i.e., sleepiness and anxiolysis).

The precise mechanism of the analgesic action is unknown. However, specific CNS opiate receptors and endogenous compounds with morphine-like activity have been identified throughout the brain and spinal cord and are likely to play a role in the expression of analgesic effects.

Morphine produces respiratory depression by direct action on brain stem respiratory centers. The mechanism of respiratory depression involves a reduction in the responsiveness of the brain stem respiratory centers to increases in carbon dioxide tension, and to electrical stimulation.

Morphine depresses the cough reflex by direct effect on the cough center in the medulla. Antitussive effects may occur with doses lower than those usually required for analgesia. Morphine causes miosis, even in total darkness. Pinpoint pupils are a sign of narcotic overdose but are not pathognomonic (e.g., pontine lesions of hemorrhagic or ischemic origins may produce similar findings). Marked mydriasis rather than miosis may be seen with worsening hypoxia.

Gastrointestinal Tract and Other Smooth Muscle

Gastric, biliary and pancreatic secretions are decreased by morphine. Morphine causes a reduction in motility associated with an increase in tone in the antrum of the stomach and duodenum. Digestion of food in the small intestine is delayed and propulsive contractions are decreased. Propulsive peristaltic waves in the colon are decreased, while tone is increased to the point of spasm. The end result is constipation. Morphine can cause a marked increase in biliary tract pressure as a result of spasm of sphincter of Oddi.

Cardiovascular System

Morphine produces peripheral vasodilation which may result in orthostatic hypotension. Release of histamine can occur and may contribute to narcotic-induced hypotension. Manifestations of histamine release and/or peripheral vasodilation may include pruritus, flushing, red eyes and sweating.

Plasma Level-Analgesia Relationships

In any particular patient, both analgesic effects and plasma morphine concentrations are related to the morphine dose. In non-tolerant individuals, plasma morphine concentration-efficacy relationships have been demonstrated and suggest that opiate receptors occupy effector compartments, leading to a lag-time, or hysteresis, between rapid changes in plasma morphine concentrations and the effects of such changes. The most direct and predictable concentration-effect relationships can, therefore, be expected at distribution equilibrium and/or steady state conditions. In general, the minimum effective analgesic concentration in the plasma of non-tolerant patients ranges from approximately 5 to 20 ng/mL.

While plasma morphine-efficacy relationships can be demonstrated in non-tolerant individuals, they are influenced by a wide variety of factors and are not generally useful as a guide to the clinical use of morphine. The effective dose in opioid-tolerant patients may be 10-50 times as great (or greater) than the appropriate dose for opioid-naive individuals. Dosages of morphine should be chosen and must be titrated on the basis of clinical evaluation of the patient and the balance between therapeutic and adverse effects.

For any fixed dose and dosing interval, morphine sulfate extended-release will have at steady state, a lower Cmax and a higher Cmin than conventional morphine. This is a potential advantage; a reduced fluctuation in morphine concentration during the dosing interval should keep morphine blood levels more centered within the theoretical “therapeutic window.” (Fluctuation for a dosing interval is defined as [Cmax-Cmin]/[Css-average].) On the other hand, the degree of fluctuation in serum morphine concentration might conceivably affect other phenomena. For example, reduced fluctuations in blood morphine concentrations might influence the rate of tolerance induction.

The elimination of morphine occurs primarily as renal excretion of 3-morphine glucuronide. A small amount of the glucuronide conjugate is excreted in the bile, and there is some minor enterohepatic recycling. Because morphine is primarily metabolized to inactive metabolites, the effects of renal disease on morphine’s elimination are not likely to be pronounced. However, as with any drug, caution should be taken to guard against unanticipated accumulation if renal and/or hepatic function is seriously impaired.

INDICATIONS AND USAGE

Morphine sulfate extended-release tablets are a controlled release oral morphine formulation indicated for the relief of moderate to severe pain. They are intended for use in patients who require repeated dosing with potent opioid analgesics over periods of more than a few days.

CONTRAINDICATIONS

Morphine sulfate extended-release is contraindicated in patients with known hypersensitivity to the drug, in patients with respiratory depression in the absence of resuscitative equipment, and in patients with acute or severe bronchial asthma.

Morphine sulfate extended-release is contraindicated in any patient who has or is suspected of having a paralytic ileus.

WARNINGS

(See also: CLINICAL PHARMACOLOGY)

Impaired Respiration

Respiratory depression is the chief hazard of all morphine preparations. Respiratory depression occurs most frequently in the elderly and debilitated patients as well as in those suffering from conditions accompanied by hypoxia or hypercapnia when even moderate therapeutic doses may dangerously decrease pulmonary ventilation.

Morphine should be used with extreme caution in patients with chronic obstructive pulmonary disease or cor pulmonale, and in patients having a substantially decreased respiratory reserve, hypoxia, hypercapnia, or pre-existing respiratory depression. In such patients, even usual therapeutic doses of morphine may decrease respiratory drive while simultaneously increasing airway resistance to the point of apnea.

Head Injury and Increased Intracranial Pressure

The respiratory depressant effects of morphine with carbon dioxide retention and secondary elevation of cerebrospinal fluid pressure may be markedly exaggerated in the presence of head injury, other intracranial lesions, or pre-existing increase in intracranial pressure. Morphine produces effects which may obscure neurologic signs of further increases in pressure in patients with head injuries.

Hypotensive Effect

Morphine sulfate extended-release, like all opioid analgesics, may cause severe hypotension in an individual whose ability to maintain his blood pressure has already been compromised by a depleted blood volume, or a concurrent administration of drugs such as phenothiazines or general anesthetics. (See also: PRECAUTIONS: Drug Interactions.) Morphine sulfate extended-release may produce orthostatic hypotension in ambulatory patients.

Morphine sulfate extended-release, like all opioid analgesics, should be administered with caution to patients in circulatory shock, since vasodilation produced by the drug may further reduce cardiac output and blood pressure.

Interactions with Other CNS Depressants

Morphine sulfate extended-release tablets, like all opioid analgesics, should be used with great caution and in reduced dosage in patients who are concurrently receiving other central nervous system depressants including sedatives or hypnotics, general anesthetics, phenothiazines, other tranquilizers and alcohol because respiratory depression, hypotension and profound sedation or coma may result.

Interactions With Mixed Agonist/Antagonist Opioid Analgesics

From a theoretical perspective, agonist/antagonist analgesics (i.e., pentazocine, nalbuphine, butorphanol and buprenorphine) should NOT be administered to a patient who has received or is receiving a course of therapy with a pure opioid agonist analgesic. In these patients, mixed agonist/antagonist analgesics may reduce the analgesic effect or may precipitate withdrawal symptoms.

Drug Dependence

Morphine can produce drug dependence and has a potential for being abused. Tolerance as well as psychological and physical dependence may develop upon repeated administration. Physical dependence, however, is not of paramount importance in the management of terminally ill patients or any patients in severe pain. Abrupt cessation or a sudden reduction in dose after prolonged use may result in withdrawal symptoms. After prolonged exposure to opioid analgesics, if withdrawal is necessary, it must be undertaken gradually. (See DRUG ABUSE AND DEPENDENCE.)

Infants born to mothers physically dependent on opioid analgesics may also be physically dependent and exhibit respiratory depression and withdrawal symptoms. (See DRUG ABUSE AND DEPENDENCE.)

Other

Although extremely rare, cases of anaphylaxis have been reported.

PRECAUTIONS

(See also: CLINICAL PHARMACOLOGY)

General

Morphine sulfate extended-release tablets are intended for use in patients who require more than several days continuous treatment with a potent opioid analgesic. The extended-release nature of the formulation allows it to be administered on a more convenient schedule than conventional immediate-release oral morphine products. (See CLINICAL PHARMACOLOGY: “Metabolism and Pharmacokinetics.”) However, morphine sulfate extended-release tablets do not release morphine continuously over the course of a dosing interval. The administration of single doses of morphine sulfate extended-release tablets on a q12h dosing schedule will result in higher peak and lower trough plasma levels than those that occur when an identical daily dose of morphine is administered using conventional oral formulations on a q4h regimen. The clinical significance of greater fluctuations in morphine plasma level has not been systematically evaluated. (See DOSAGE AND ADMINISTRATION.)

As with any potent opioid, it is critical to adjust the dosing regimen for each patient individually, taking into account the patient’s prior analgesic treatment experience. Although it is clearly impossible to enumerate every consideration that is important to the selection of the initial dose and dosing interval of morphine sulfate extended-release tablets, attention should be given to 1) the daily dose, potency, and characteristics of the opioid the patient has been taking previously (e.g., whether it is a pure agonist or mixed agonist-antagonist), 2) the reliability of the relative potency estimate used to calculate the dose of morphine needed [N.B. potency estimates may vary with the route of administration], 3) the degree of opioid tolerance, if any, and 4) the general condition and medical status of the patient.

Selection of patients for treatment with morphine sulfate extended-release tablets should be governed by the same principles that apply to the use of morphine or other potent opioid analgesics. Specifically, the increased risks associated with its use in the following populations should be considered: the elderly or debilitated and those with severe impairment of hepatic, pulmonary or renal function; myxedema or hypothyroidism; adrenocortical insufficiency (e.g., Addison’s Disease); CNS depression or coma; toxic psychosis; prostatic hypertrophy or urethral stricture; acute alcoholism; delirium tremens; kyphoscoliosis, or inability to swallow.

The administration of morphine, like all opioid analgesics, may obscure the diagnosis or clinical course in patients with acute abdominal conditions.

Morphine may aggravate pre-existing convulsions in patients with convulsive disorders. Morphine should be used with caution in patients about to undergo surgery of the biliary tract since it may cause spasm of the sphincter of Oddi. Similarly, morphine should be used with caution in patients with acute pancreatitis secondary to biliary tract disease.

Information for Patients

If clinically advisable, patients receiving morphine sulfate extended-release tablets should be given the following instructions by the physician:

1. Appropriate pain management requires changes in the dose to maintain best pain control. Patients should be advised of the need to contact their physician if pain control is inadequate, but not to change the dose of morphine sulfate extended-release tablets without consulting their physician.
2. Morphine may impair mental and/or physical ability required for the performance of potentially hazardous tasks (e.g., driving, operating machinery). Patients started on morphine sulfate extended-release tablets or whose dose has been changed should refrain from dangerous activity until it is established that they are not adversely affected.
3. Morphine should not be taken with alcohol or other CNS depressants (sleep aids, tranquilizers) because additive effects including CNS depression may occur. A physician should be consulted if other prescription medications are currently being used or are prescribed for future use.
4. For women of childbearing potential who become or are planning to become pregnant, a physician should be consulted regarding analgesics and other drug use.
5. Upon completion of therapy, it may be appropriate to taper the morphine dose, rather than abruptly discontinue it.
6. While psychological dependence (“addiction”) to morphine used in the treatment of pain is very rare, morphine is one of a class of drugs known to be abused and should be handled accordingly.

Drug Interactions

(See WARNINGS)

The concomitant use of other central nervous system depressants including sedatives or hypnotics, general anesthetics, phenothiazines, tranquilizers and alcohol may produce additive depressant effects. Respiratory depression, hypotension and profound sedation or coma may occur. When such combined therapy is contemplated, the dose of one or both agents should be reduced. Opioid analgesics, including morphine sulfate extended-release tablets, may enhance the neuromuscular blocking action of skeletal muscle relaxants and produce an increased degree of respiratory depression.

Carcinogenicity/Mutagenicity/Impairment of Fertility

Studies of morphine sulfate extended-release in animals to evaluate the drug’s carcinogenic and mutagenic potential or the effect on fertility have not been conducted.

Pregnancy

Teratogenic Effects-Category C: Adequate animal studies on reproduction have not been performed to determine whether morphine affects fertility in males or females. There are no well-controlled studies in women, but marketing experience does not include any evidence of adverse effects on the fetus following routine (short-term) clinical use of morphine sulfate products. Although there is no clearly defined risk, such experience cannot exclude the possibility of infrequent or subtle damage to the human fetus.

Morphine sulfate extended-release tablets should be used in pregnant women only when clearly needed. (See also: PRECAUTIONS: Labor and Delivery, and DRUG ABUSE AND DEPENDENCE.)

Nonteratogenic effects: Infants born from mothers who have been taking morphine chronically may exhibit withdrawal symptoms.

Labor and Delivery

Morphine sulfate extended-release tablets are not recommended for use in women during and immediately prior to labor. Occasionally, opioid analgesics may prolong labor through actions which temporarily reduce the strength, duration and frequency of uterine contractions. However, this effect is not consistent and may be offset by an increased rate of cervical dilatation which tends to shorten labor.

Neonates whose mothers received opioid analgesics during labor should be observed closely for signs of respiratory depression. A specific narcotic antagonist, naloxone, should be available for reversal of narcotic-induced respiratory depression in the neonate.

Nursing Mothers

Low levels of morphine have been detected in the breast milk. Withdrawal symptoms can occur in breast-feeding infants when maternal administration of morphine sulfate extended-release is stopped. Ordinarily, nursing should not be undertaken while a patient is receiving morphine sulfate extended-release tablets since morphine may be excreted in the milk.

Pediatric Use

Use of morphine sulfate extended-release tablets has not been evaluated systematically in pediatric patients.

Geriatric Use

Clinical studies of morphine sulfate extended-release tablets did not include sufficient numbers of subjects aged 65 and over to determine whether they respond differently from younger subjects. Other reported clinical experience has not identified differences in responses between the elderly and younger patients. In general, dose selection for an elderly patient should be cautious, usually starting at the low end of the dosing range, reflecting the greater frequency of decreased hepatic, renal, or cardiac function, and of concomitant disease or other drug therapy.

ADVERSE REACTIONS

The adverse reactions caused by morphine are essentially those observed with other opioid analgesics. They include the following major hazards: respiratory depression, apnea, and to a lesser degree, circulatory depression; respiratory arrest, shock and cardiac arrest.

Most Frequently Observed

Constipation, lightheadedness, dizziness, sedation, nausea, vomiting, sweating, dysphoria and euphoria. Some of these effects seem to be more prominent in ambulatory patients and in those not experiencing severe pain. Some adverse reactions in ambulatory patients may be alleviated if the patient lies down.

Less Frequently Observed Reactions

Central Nervous System: Weakness, headache, agitation, tremor, uncoordinated muscle movements, seizure, alterations of mood (nervousness, apprehension, depression, floating feelings), dreams, muscle rigidity, transient hallucinations and disorientation, visual disturbances, insomnia and increased intracranial pressure.

Gastrointestinal: Dry mouth, constipation, biliary tract spasm, laryngospasm, anorexia, diarrhea, cramps, taste alteration, ileus, and intestinal obstruction.

Cardiovascular: Flushing of the face, chills, tachycardia, bradycardia, palpitation, faintness, syncope, hypotension and hypertension.

Genitourinary: Urine retention or hesitance, reduced libido and/or potency.

Dermatologic: Pruritus, urticaria, other skin rashes, edema and diaphoresis.

Other: Antidiuretic effect, paresthesia, muscle tremor, blurred vision, nystagmus, diplopia, miosis, and anaphylaxis.

DRUG ABUSE AND DEPENDENCE

Opioid analgesics may cause psychological and physical dependence (see WARNINGS). Physical dependence results in withdrawal symptoms in patients who abruptly discontinue the drug or may be precipitated through the administration of drugs with narcotic antagonist activity, e.g., naloxone or mixed agonist/antagonist analgesics (pentazocine, etc.; see also OVERDOSAGE). Physical dependence usually does not occur to a clinically significant degree until after several weeks of continued narcotic usage. Tolerance, in which increasingly large doses are required in order to produce the same degree of analgesia, is initially manifested by a shortened duration of analgesic effect, and, subsequently, by decreases in the intensity of analgesia.

In chronic-pain patients, and in narcotic-tolerant cancer patients, the administration of morphine sulfate extended-release tablets should be guided by the degree of tolerance manifested. Physical dependence, per se, is not ordinarily a concern when one is dealing with opioid-tolerant patients whose pain and suffering is associated with an irreversible illness.

If morphine sulfate extended-release tablets are abruptly discontinued, a moderate to severe abstinence syndrome may occur. The opioid agonist abstinence syndrome is characterized by some or all of the following: restlessness, lacrimation, rhinorrhea, yawning, perspiration, gooseflesh, restless sleep or “yen” and mydriasis during the first 24 hours. These symptoms often increase in severity and over the next 72 hours may be accompanied by increasing irritability, anxiety, weakness, twitching and spasms of muscles; kicking movements; severe backache, abdominal and leg pains; abdominal and muscle cramps; hot and cold flashes, insomnia, nausea, anorexia, vomiting, intestinal spasm, diarrhea; coryza and repetitive sneezing; increase in body temperature, blood pressure, respiratory rate and heart rate. Because of excessive loss of fluids through sweating, vomiting and diarrhea, there is usually marked weight loss, dehydration, ketosis, and disturbances in acid-base balance. Cardiovascular collapse can occur. Without treatment most observable symptoms disappear in 5 to 14 days; however, there appears to be a phase of secondary or chronic abstinence which may last for 2 to 6 months characterized by insomnia, irritability, and muscular aches.

If treatment of physical dependence of patients on morphine sulfate extended-release tablets is necessary, the patient may be detoxified by gradual reduction of the dosage. Gastrointestinal disturbances or dehydration should be treated accordingly.

OVERDOSAGE

Acute overdosage with morphine is manifested by respiratory depression, somnolence progressing to stupor or coma, skeletal muscle flaccidity, cold and clammy skin, constricted pupils, and, sometimes, bradycardia, hypotension and death.

In the treatment of overdosage, primary attention should be given to the re-establishment of a patent airway and institution of assisted or controlled ventilation. The pure opioid antagonist naloxone, is a specific antidote against respiratory depression which results from opioid overdose. Naloxone (usually 0.4 to 2 mg) should be administered intravenously; however, because its duration of action is relatively short, the patient must be carefully monitored until spontaneous respiration is reliably re-established. If the response to naloxone is suboptimal or not sustained, additional naloxone may be administered, as needed, or given by continuous infusion to maintain alertness and respiratory function; however, there is no information available about the cumulative dose of naloxone that may be safely administered.

Naloxone should not be administered in the absence of clinically significant respiratory or circulatory depression secondary to morphine overdose. Naloxone should be administered cautiously to persons who are known, or suspected to be physically dependent on morphine sulfate extended-release tablets. In such cases, an abrupt or complete reversal of narcotic effects may precipitate an acute abstinence syndrome.

Note: In an individual physically dependent on opioids, administration of the usual dose of the antagonist will precipitate an acute withdrawal syndrome. The severity of the withdrawal syndrome produced will depend on the degree of physical dependence and the dose of the antagonist administered. Use of a narcotic antagonist in such a person should be avoided. If necessary to treat serious respiratory depression in the physically dependent patient, the antagonist should be administered with care and by titration with smaller than usual doses of the antagonist.

Supportive measures (including oxygen, vasopressors) should be employed in the management of circulatory shock and pulmonary edema accompanying overdose as indicated. Cardiac arrest of arrhythmias may require cardiac massage or defibrillation.

DOSAGE AND ADMINISTRATION

(See also: CLINICAL PHARMACOLOGY, WARNINGS and PRECAUTIONS sections)

MORPHINE SULFATE EXTENDED-RELEASE TABLETS ARE TO BE TAKEN WHOLE, AND ARE NOT TO BE BROKEN, CHEWED OR CRUSHED.

TAKING BROKEN, CHEWED OR CRUSHED MORPHINE SULFATE EXTENDED-RELEASE TABLETS COULD LEAD TO THE RAPID RELEASE AND ABSORPTION OF A POTENTIALLY TOXIC DOSE OF MORPHINE.

Morphine sulfate extended-release tablets are intended for use in patients who require more than several days continuous treatment with a potent opioid analgesic. The extended-release nature of the formulation allows it to be administered on a more convenient schedule than conventional immediate-release oral morphine products. (See CLINICAL PHARMACOLOGY: “Metabolism and Pharmacokinetics.”) However, morphine sulfate extended-release tablets do not release morphine continuously over the course of a dosing interval. The administration of single doses of morphine sulfate extended-release tablets on a q12h dosing schedule will result in higher peak and lower trough plasma levels than those that occur when an identical daily dose of morphine is administered using conventional oral formulations on a q4h regimen. The clinical significance of greater fluctuations in morphine plasma level has not been systematically evaluated.

As with any potent opioid drug product, it is critical to adjust the dosing regimen for each patient individually, taking into account the patient’s prior analgesic treatment experience. Although it is clearly impossible to enumerate every consideration that is important to the selection of initial dose and dosing interval of morphine sulfate extended-release tablets attention should be given to 1) the daily dose, potency and precise characteristics of the opioid the patient has been taking previously (e.g., whether it is a pure agonist or mixed agonist/antagonist), 2) the reliability of the relative potency estimate used to calculate the dose of morphine needed [N.B. potency estimates may vary with the route of administration], 3) the degree of opioid tolerance, if any, and 4) the general condition and medical status of the patient.

The following dosing recommendations, therefore, can only be considered suggested approaches to what is actually a series of clinical decisions in the management of the pain of an individual patient.

Conversion from Conventional Oral Morphine to Morphine Sulfate Extended-Release Tablets

A patient’s daily morphine requirement is established using immediate-release oral morphine (dosing every 4 to 6 hours). The patient is then converted to morphine sulfate extended-release tablets in either of two ways: 1) by administering one-half of the patient’s 24-hour requirement as morphine sulfate extended-release tablets on an every 12-hour schedule; or, 2) by administering one-third of the patient’s daily requirement as morphine sulfate extended-release tablets on an every eight hour schedule. With either method, dose and dosing interval is then adjusted as needed (see discussion below). The 15 mg tablet should be used for initial conversion for patients whose total daily requirement is expected to be less than 60 mg. The 30 mg tablet strength is recommended for patients with a daily morphine requirement of 60 to 120 mg. When the total daily dose is expected to be greater than 120 mg, the appropriate combination of tablet strengths should be employed.

Conversion from Parenteral Morphine or Other Opioids (Parenteral or Oral) to Morphine Sulfate Extended-Release Tablets

Morphine sulfate extended-release tablets can be administered as the initial oral morphine drug product; in this case, however, particular care must be exercised in the conversion process. Because of uncertainty about, and intersubject variation in, relative estimates of opioid potency and cross tolerance, initial dosing regimens should be conservative; that is, an underestimation of the 24-hour oral morphine requirement is preferred to an overestimate. To this end, initial individual doses of morphine sulfate extended-release tablets should be estimated conservatively. In patients whose daily morphine requirements are expected to be less than or equal to 120 mg per day, the 30 mg tablet strength is recommended for the initial titration period. Once a stable dose regimen is reached, the patient can be converted to the 60 mg or 100 mg tablet strength, or an appropriate combination of tablet strengths, if desired.

Estimates of the relative potency of opioids are only approximate and are influenced by route of administration, individual patient differences, and possibly, by an individual’s medical condition. Consequently, it is difficult to recommend any fixed rule for converting a patient to morphine sulfate extended-release tablets directly. The following general points should be considered, however.

1. Parenteral to oral morphine ratio: Estimates of the oral to parenteral potency of morphine vary. Some authorities suggest that a dose of oral morphine only three times the daily parenteral morphine requirement may be sufficient in chronic use settings.
2. Other Parenteral or oral opioids to oral morphine: Because there is lack of systematic evidence bearing on these types of analgesic substitutions, specific recommendations are not possible.

Physicians are advised to refer to published relative potency data, keeping in mind that such ratios are only approximate. In general, it is safer to underestimate the daily dose of morphine sulfate extended-release tablets required and rely upon ad hoc supplementation to deal with inadequate analgesia. (See discussion which follows.)

Use of Morphine Sulfate Extended-Release Tablets as the first opioid analgesic

There has been no systematic evaluation of morphine sulfate extended-release tablets as an initial opioid analgesic in the management of pain. Because it may be more difficult to titrate a patient using a controlled-release morphine, it is ordinarily advisable to begin treatment using an immediate-release formulation.

Considerations in the Adjustment of Dosing Regimens

Whatever the approach, if signs of excessive opioid effects are observed early in a dosing interval, the next dose should be reduced. If this adjustment leads to inadequate analgesia, that is, “breakthrough” pain occurs late in the dosing interval, the dosing interval may be shortened. Alternatively, a supplemental dose of a short-acting analgesic may be given. As experience is gained, adjustments can be made to obtain an appropriate balance between pain relief, opioid side effects, and the convenience of the dosing schedule.

In adjusting dosing requirements, it is recommended that the dosing interval never be extended beyond 12 hours because the administration of very large single doses may lead to acute overdose. (N.B. morphine sulfate extended-release tablets are a controlled-release formulation; it does not release morphine continuously over the dosing interval.)

For patients with low daily morphine requirements, the 15 mg tablet should be used.

Conversion from Morphine Sulfate Extended-Release Tablets to Parenteral Opioids:

When converting a patient from morphine sulfate extended-release tablets to parenteral opioids, it is best to assume that the parenteral to oral potency is high. NOTE THAT THIS IS THE CONVERSE OF THE STRATEGY USED WHEN THE DIRECTION OF CONVERSION IS FROM THE PARENTERAL TO ORAL FORMULATIONS. IN BOTH CASES, HOWEVER, THE AIM IS TO ESTIMATE THE NEW DOSE CONSERVATIVELY. For example, to estimate the required 24-hour dose of morphine sulfate for IM use, one could employ a conversion of 1 mg of morphine sulfate IM for every 6 mg of morphine sulfate as morphine sulfate extended-release tablets. Of course, the IM 24-hour dose would have to be divided by six and administered on a q4h regimen. This approach is recommended because it is least likely to cause overdose.

Safety and Handling

MORPHINE SULFATE EXTENDED-RELEASE TABLETS ARE TO BE TAKEN WHOLE, AND ARE NOT TO BE BROKEN, CHEWED, OR CRUSHED. TAKING BROKEN, CHEWED, OR CRUSHED MORPHINE SULFATE EXTENDED-RELEASE TABLETS COULD LEAD TO THE RAPID RELEASE AND ABSORPTION OF A POTENTIALLY TOXIC DOSE OF MORPHINE.

HOW SUPPLIED

Morphine Sulfate Extended-Release Tablets, 100 mg are gray, round standard cup film coated tablets, debossed WATSON over 617 on one side and plain on the other side supplied in bottles of 100 and 500.

Store at controlled room temperature 15°-30°C (59°-86°F). [See USP.]

Dispense in a tight, light-resistant container as defined in the USP.

CAUTION

DEA Order Form Required.

Watson Laboratories, Inc.
Corona, CA 92880 USA